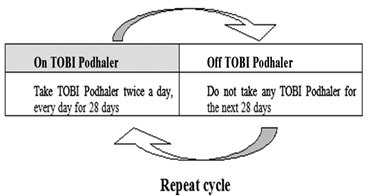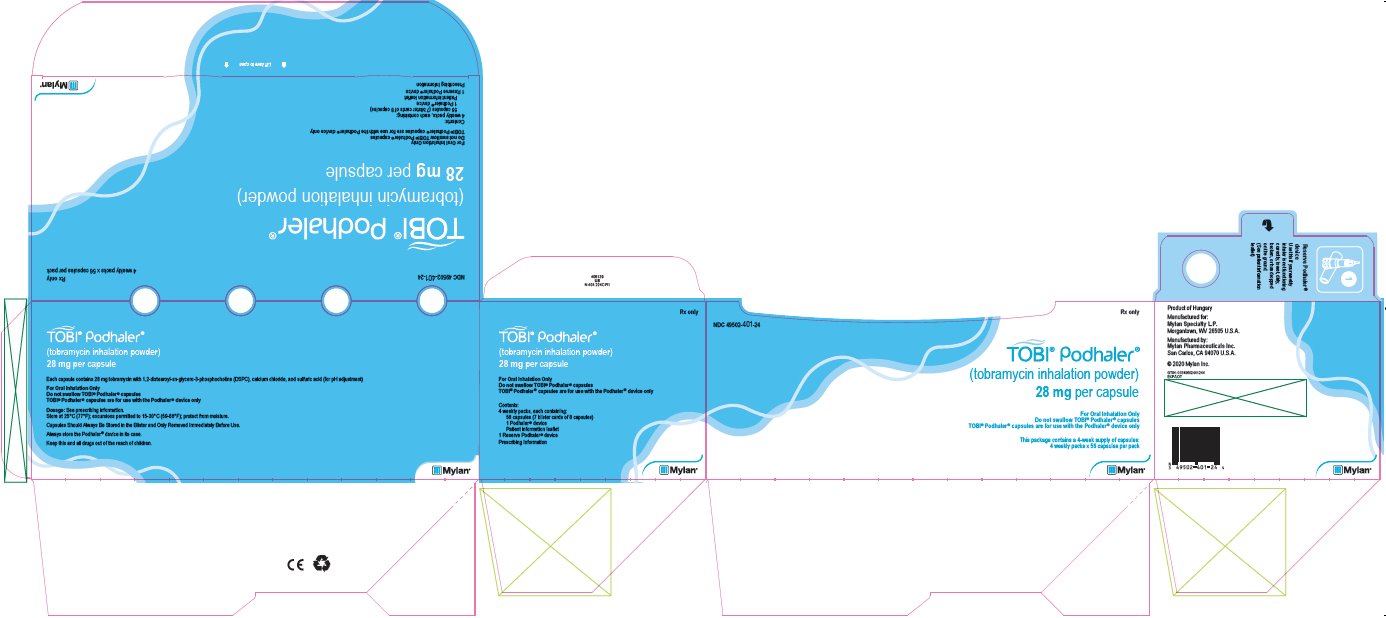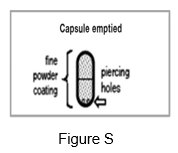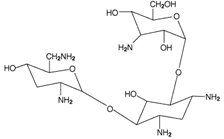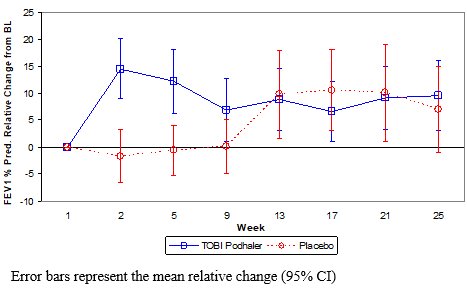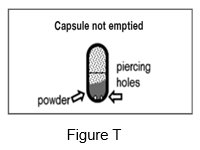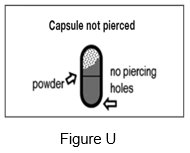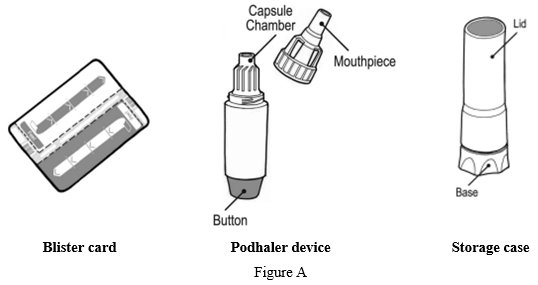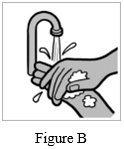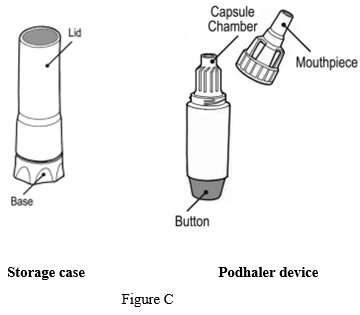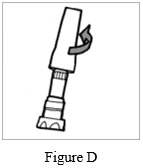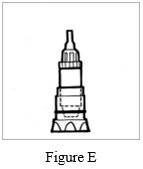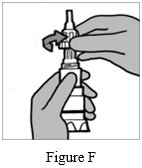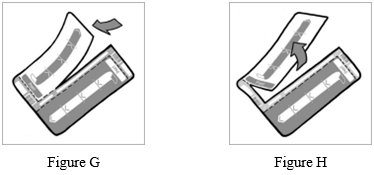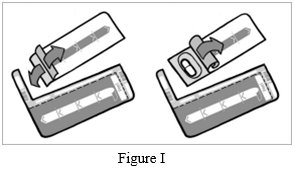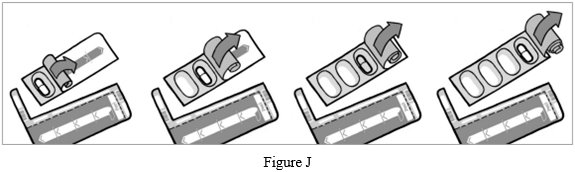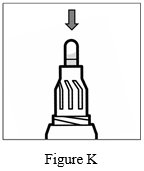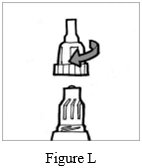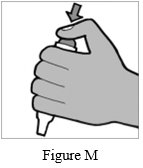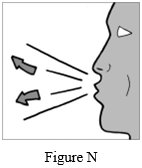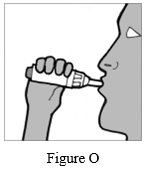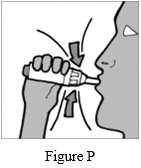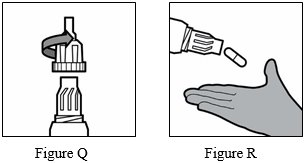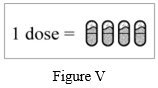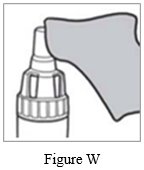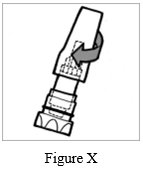 DRUG LABEL: TOBI Podhaler
NDC: 49502-401 | Form: CAPSULE
Manufacturer: Viatris Specialty LLC
Category: prescription | Type: HUMAN PRESCRIPTION DRUG LABEL
Date: 20230215

ACTIVE INGREDIENTS: TOBRAMYCIN 28 mg/1 1
INACTIVE INGREDIENTS: 1,2-DISTEAROYL-SN-GLYCERO-3-PHOSPHOCHOLINE; CALCIUM CHLORIDE; SULFURIC ACID

HIGHLIGHTS OF PRESCRIBING INFORMATION

These highlights do not include all the information needed to use TOBI PODHALER safely and effectively. See full prescribing information for TOBI PODHALER.
TOBI® PODHALER® (tobramycin inhalation powder), for oral inhalation use
Initial U.S. Approval: 1975

RECENT MAJOR CHANGES

Warnings and Precautions, Ototoxicity (5.2) 2/2023

1 INDICATIONS AND USAGE

TOBI Podhaler is an aminoglycoside antibacterial indicated for the management of cystic fibrosis patients with Pseudomonas aeruginosa.

Safety and efficacy have not been demonstrated in patients under the age of 6 years, patients with forced expiratory volume in 1 second (FEV1) <25% or >80%, or patients colonized with Burkholderia cepacia (1)

2 DOSAGE AND ADMINISTRATION

- DO NOT swallow TOBI Podhaler capsules (2)
- For use with the Podhaler device only (2)
- For oral inhalation only (2)
- The recommended dosage is the inhalation of four 28 mg capsules twice-daily for 28 days (2)

3 DOSAGE FORMS AND STRENGTHS

Inhalation powder: 28 mg in a capsule (3)

4 CONTRAINDICATIONS

Known hypersensitivity to any aminoglycoside (4)

5 WARNINGS AND PRECAUTIONS

- Caution should be exercised when prescribing TOBI Podhaler to patients with known or suspected auditory, vestibular, renal, or neuromuscular dysfunction (5.2, 5.3, 5.4)
- Ototoxicity, as measured by complaints of hearing loss or tinnitus, was reported in clinical trials (5.2)
- Aminoglycosides may aggravate muscle weakness because of a potential curare-like effect on neuromuscular function (5.6)
- Bronchospasm can occur with inhalation of TOBI Podhaler (5.1)
- Audiograms, serum concentrations, and renal function should be monitored as appropriate (5.3, 5.5, 5.6)
- Embryo-Fetal Toxicity: Aminoglycosides can cause fetal harm Apprise women of the potential hazard to the fetus (5.6, 8.1)

6 ADVERSE REACTIONS

The most common adverse reactions (≥10 % of TOBI Podhaler and TOBI patients in primary safety population) are cough, lung disorder, productive cough, dyspnea, pyrexia, oropharyngeal pain, dysphonia, hemoptysis, and headache (6.1)

To report SUSPECTED ADVERSE REACTIONS, contact Mylan at 1-877-446-3679 (1-877-4-INFO-RX) or FDA at 1-800-FDA-1088 or www.fda.gov/medwatch.

7 DRUG INTERACTIONS

Concurrent and/or sequential use of TOBI Podhaler with other drugs with neurotoxic, nephrotoxic, or ototoxic potential should be avoided (7)

FULL PRESCRIBING INFORMATION

1 INDICATIONS AND USAGE

TOBI Podhaler is indicated for the management of cystic fibrosis patients with Pseudomonas aeruginosa.

Safety and efficacy have not been demonstrated in patients under the age of 6 years, patients with forced expiratory volume in 1 second (FEV1) <25% or >80% predicted, or patients colonized with Burkholderia cepacia [see Clinical Studies (14)].

2 DOSAGE AND ADMINISTRATION

DO NOT SWALLOW TOBI PODHALER CAPSULES

FOR USE WITH THE PODHALER DEVICE ONLY

FOR ORAL INHALATION ONLY

TOBI Podhaler capsules must not be swallowed as the intended effects in the lungs will not be obtained. The contents of TOBI Podhaler capsules are only for oral inhalation and should only be used with the Podhaler device.

The recommended dosage of TOBI Podhaler for both adults and pediatric patients 6 years of age and older is the inhalation of the contents of four 28 mg TOBI Podhaler capsules twice-daily for 28 days using the Podhaler device.

Refer to the Instructions For Use (IFU) for full administration information.

Dosage is not adjusted by weight. Each dose of four capsules should be taken as close to 12 hours apart as possible; each dose should not be taken less than 6 hours apart.

TOBI Podhaler is administered twice-daily in alternating periods of 28 days. After 28 days of therapy, patients should stop TOBI Podhaler therapy for the next 28 days, and then resume therapy for the next 28-day on and 28-day off cycle.

TOBI Podhaler capsules should always be stored in the blister and each capsule should only be removed IMMEDIATELY BEFORE USE.

For patients taking several different inhaled medications and/or performing chest physiotherapy, the order of therapies should follow the physician’s recommendation. It is recommended that TOBI Podhaler is taken last.

3 DOSAGE FORMS AND STRENGTHS

Inhalation powder:

28 mg: clear, colorless hypromellose capsule with “MYL TPH” in blue radial imprint on one part of the capsule and the Mylan logo in blue radial imprint on the other part of the capsule.

4 CONTRAINDICATIONS

TOBI Podhaler is contraindicated in patients with a known hypersensitivity to any aminoglycoside.

5 WARNINGS AND PRECAUTIONS

5.1 Bronchospasm

Bronchospasm has been reported with inhalation of TOBI Podhaler [see Adverse Reactions (6.1)]. Bronchospasm should be treated as medically appropriate.

5.2 Ototoxicity

Ototoxicity with use of TOBI Podhaler

Caution should be exercised when prescribing TOBI Podhaler to patients with known or suspected auditory or vestibular dysfunction.

Ototoxicity, as measured by complaints of hearing loss or tinnitus, was reported by patients in the TOBI Podhaler clinical studies [see Adverse Reactions (6.1)]. Tinnitus may be a sentinel symptom of ototoxicity, and therefore the onset of this symptom warrants caution. Ototoxicity, manifested as both auditory (hearing loss) and vestibular toxicity, has been reported with parenteral aminoglycosides. Vestibular toxicity may be manifested by vertigo, ataxia or dizziness.

Risk of Ototoxicity Due to Mitochondrial DNA Variants

Cases of ototoxicity with aminoglycosides have been observed in patients with certain variants in the mitochondrially encoded 12S rRNA gene (MT-RNR1), particularly the m.1555A>G variant. Ototoxicity occurred in some patients even when their aminoglycoside serum levels were within the recommended range. Mitochondrial DNA variants are present in less than 1% of the general US population, and the proportion of the variant carriers who may develop ototoxicity as well as the severity of ototoxicity is unknown. In case of known maternal history of ototoxicity due to aminoglycoside use or a known mitochondrial DNA variant in the patient, consider alternative treatments other than aminoglycosides unless the increased risk of permanent hearing loss is outweighed by the severity of infection and lack of safe and effective alternative therapies.

5.3 Nephrotoxicity

Caution should be exercised when prescribing TOBI Podhaler to patients with known or suspected renal dysfunction.

Nephrotoxicity was not observed during TOBI Podhaler clinical studies but has been associated with aminoglycosides as a class.

5.4 Neuromuscular Disorders

Caution should be exercised when prescribing TOBI Podhaler to patients with known or suspected neuromuscular dysfunction.

TOBI Podhaler should be used cautiously in patients with neuromuscular disorders, such as myasthenia gravis or Parkinson’s disease, since aminoglycosides may aggravate muscle weakness because of a potential curare-like effect on neuromuscular function.

5.5 Embryo-Fetal Toxicity

Aminoglycosides can cause fetal harm when administered to a pregnant woman. Aminoglycosides cross the placenta, and streptomycin has been associated with several reports of total, irreversible, bilateral congenital deafness in pediatric patients exposed in utero. However, systemic absorption of tobramycin following inhaled administration is expected to be minimal [see Clinical Pharmacology (12.3)]. Patients who use TOBI Podhaler during pregnancy, or become pregnant while taking TOBI Podhaler should be apprised of the potential hazard to the fetus [see Use in Specific Populations (8.1)].

5.6 Concomitant Use of Systemic Aminoglycosides

Patients receiving concomitant TOBI and parenteral aminoglycoside therapy should be monitored as clinically appropriate for toxicities associated with aminoglycosides as a class. Serum tobramycin levels should be monitored.

6 ADVERSE REACTIONS

6.1 Clinical Trials Experience

Because clinical trials are conducted under widely varying conditions, adverse reaction rates observed in the clinical trials of a drug cannot be directly compared to rates in the clinical trials of another drug and may not reflect the rates observed in practice.

TOBI Podhaler has been evaluated for safety in 425 cystic fibrosis patients exposed to at least one dose of TOBI Podhaler, including 273 patients who were exposed across three cycles (6 months) of treatment. Each cycle consisted of 28 days on-treatment (with 112 mg administered twice-daily) and 28 days off-treatment. Patients with serum creatinine ≥2 mg/dL and blood urea nitrogen (BUN) ≥40 mg/dL were excluded from clinical studies. There were 218 males and 207 females in this population, and reflecting the cystic fibrosis population in the U.S., the vast majority of patients were Caucasian. There were 221 patients ≥20 years old, 121 patients ≥13 to <20 years old, and 83 patients ≥6 to <13 years old. There were 239 patients with screening FEV1 % predicted ≥50%, 156 patients with screening FEV1 % predicted <50%, and 30 patients with missing FEV1 % predicted.

The primary safety population reflects patients from Study 1, an open-label study comparing TOBI Podhaler with TOBI (tobramycin inhalation solution, USP) over three cycles of 4 weeks on treatment followed by 4 weeks off treatment. Randomization, in a planned 3:2 ratio, resulted in 308 patients treated with TOBI Podhaler and 209 patients treated with TOBI. For both the TOBI Podhaler and TOBI groups, mean exposure to medication for each cycle was 28 to 29 days. The mean age for both arms was between 25 and 26 years old. The mean baseline FEV1 % predicted for both arms was 53%.

Table 1 displays adverse drug reactions reported by at least 2% of TOBI Podhaler patients in Study 1, inclusive of all cycles (on and off treatment). Adverse drug reactions are listed according to MedDRA system organ class and sorted within system organ class group in descending order of frequency.

Table 1: Adverse Reactions Reported in Study 1 (Occurring in ≥2% of TOBI Podhaler Patients)
Primary System Organ Class Preferred Term | TOBI Podhaler N=308 % | TOBI N=209 %
Respiratory, thoracic, and mediastinal disorders
Cough | 48.4 | 31.1
Lung disorder [This includes adverse events of pulmonary or cystic fibrosis exacerbations] | 33.8 | 30.1
Productive cough | 18.2 | 19.6
Dyspnea | 15.6 | 12.4
Oropharyngeal pain | 14.0 | 10.5
Dysphonia | 13.6 | 3.8
Hemoptysis | 13.0 | 12.4
Nasal congestion | 8.1 | 7.2
Rales | 7.1 | 6.2
Wheezing | 6.8 | 6.2
Chest discomfort | 6.5 | 2.9
Throat irritation | 4.5 | 1.9
Gastrointestinal disorders
Nausea | 7.5 | 9.6
Vomiting | 6.2 | 5.7
Diarrhea | 4.2 | 1.9
Dysgeusia | 3.9 | 0.5
Infections and infestations
Upper respiratory tract infection | 6.8 | 8.6
Investigations
Pulmonary function test decreased | 6.8 | 8.1
Forced expiratory volume decreased | 3.9 | 1.0
Blood glucose increased | 2.9 | 0.5
Vascular disorders
Epistaxis | 2.6 | 1.9
Nervous system disorders
Headache | 11.4 | 12.0
General disorders and administration site conditions
Pyrexia | 15.6 | 12.4
Musculoskeletal and connective tissue disorders
Musculoskeletal chest pain | 4.5 | 4.8
Skin and subcutaneous tissue disorders
Rash | 2.3 | 2.4

Adverse drug reactions that occurred in <2% of patients treated with TOBI Podhaler in Study 1 were: bronchospasm (TOBI Podhaler 1.6%, TOBI 0.5%); deafness including deafness unilateral (reported as mild to moderate hearing loss or increased hearing loss) (TOBI Podhaler 1.0%, TOBI 0.5%); and tinnitus (TOBI Podhaler 1.9%, TOBI 2.4%).

Discontinuations in Study 1 were higher in the TOBI Podhaler arm compared to TOBI (27% TOBI Podhaler versus 18% TOBI). This was driven primarily by discontinuations due to adverse events (14% TOBI Podhaler versus 8% TOBI). Higher rates of discontinuation were seen in subjects ≥20 years old and those with baseline FEV1 % predicted <50%.

Respiratory related hospitalizations occurred in 24% of the patients in the TOBI Podhaler arm and 22% of the patients in the TOBI arm. There was an increased new usage of antipseudomonal medication in the TOBI Podhaler arm (65% TOBI Podhaler versus 55% TOBI). This included oral antibiotics in 55% of TOBI Podhaler patients and 40% of TOBI patients and intravenous antibiotics in 35% of TOBI Podhaler patients and 33% of TOBI patients. Median time to first antipseudomonal usage was 89 days in the TOBI Podhaler arm and 112 days in the TOBI arm.

The supportive safety population reflects patients from two studies: Study 2, a double-blind, placebo-controlled design for the first treatment cycle, followed by all patients receiving TOBI Podhaler (replaced placebo) for two additional cycles, and Study 3, a double-blind, placebo-controlled trial for one treatment cycle only. Placebo in these studies was inhaled powder without the active ingredient, tobramycin. The patient population for these studies was much younger than in Study 1 (mean age 13 years old).

Adverse drug reactions reported more frequently by TOBI Podhaler patients in the placebo-controlled cycle (Cycle 1) of Study 2, which included 46 TOBI Podhaler and 49 placebo patients, were:

Respiratory, thoracic, and mediastinal disorders

Pharyngolaryngeal pain (TOBI Podhaler 10.9%, placebo 0%); dysphonia (TOBI Podhaler 4.3%, placebo 0%)

Gastrointestinal disorders

Dysgeusia (TOBI Podhaler 6.5%, placebo 2.0%)

Adverse drug reactions reported more frequently by TOBI Podhaler patients in Study 3, which included 30 TOBI Podhaler and 32 placebo patients, were:

Respiratory, thoracic, and mediastinal disorders

Cough (TOBI Podhaler 10%, placebo 0%)

Ear and labyrinth disorders

Hypoacusis (TOBI Podhaler 10%, placebo 6.3%)

Audiometric Assessment

In Study 1, audiology testing was performed in a subset of approximately 25% of TOBI Podhaler (n=78) and TOBI (n=45) patients. Using the criteria for either ear of ≥10 dB loss at two consecutive frequencies, ≥20 dB loss at any frequency, or loss of response at three consecutive frequencies where responses were previously obtained, five TOBI Podhaler patients and three TOBI patients were judged to have ototoxicity, a ratio similar to the planned 3:2 randomization for this study.

Audiology testing was also performed in a subset of patients in both Study 2 (n=13 from the TOBI Podhaler group and n=9 from the placebo group) and Study 3 (n=14 from the TOBI Podhaler group and n=11 from the placebo group). In Study 2, no patients reported hearing complaints but two TOBI Podhaler patients met the criteria for ototoxicity. In Study 3, three TOBI Podhaler and two placebo patients had reports of ‘hypoacusis.’ One TOBI Podhaler and two placebo patients met the criteria for ototoxicity. In some patients, ototoxicity was transient or may have been related to a conductive defect.

Cough

Cough is a common symptom in cystic fibrosis, reported in 42% of the patients in Study 1 at baseline. Cough was the most frequently reported adverse event in Study 1 and was more common in the TOBI Podhaler arm (48% TOBI Podhaler versus 31 % TOBI). There was a higher rate of cough adverse event reporting during the first week of active treatment with TOBI Podhaler (i.e., the first week of Cycle 1). The time to first cough event in the TOBI Podhaler and TOBI groups were similar thereafter. In some patients, cough resulted in discontinuation of TOBI Podhaler treatment. Sixteen patients (5%) receiving treatment with TOBI Podhaler discontinued study treatment due to cough events compared with 2 (1%) in the TOBI treatment group. Children and adolescents coughed more than adults when treated with TOBI Podhaler, yet the adults were more likely to discontinue: of the 16 patients on TOBI Podhaler in Study 1 who discontinued treatment due to cough events, 14 were ≥20 years of age, one patient was between the ages of 13 and <20, and one was between the ages of 6 and <13. The rates of bronchospasm (as measured by ≥20% decrease in FEV1 % predicted post-dose) were approximately 5% in both treatment groups, and none of these patients experienced concomitant cough.

In Study 2, cough was the most commonly reported adverse event during the first cycle of treatment (the double blind period of treatment) and occurred more frequently in placebo-treated patients (26.5%) than patients treated with TOBI Podhaler (13%). Similar percentages of patients in both treatment groups reported cough as a baseline symptom. In Study 3, cough events were reported by three patients in the TOBI Podhaler group (10%) and none in the placebo group (0%).

6.2 Postmarketing Experience

The following adverse reactions have been identified during postapproval use of TOBI Podhaler. Because these reactions are reported voluntarily from a population of uncertain size, it is not always possible to reliably estimate their frequency or establish a causal relationship to drug exposure.

Respiratory, thoracic, and mediastinal disorders

Aphonia, Sputum discolored

General disorders and administration site conditions

Malaise

7 DRUG INTERACTIONS

No clinical drug interaction studies have been performed with TOBI Podhaler. In clinical studies, patients receiving TOBI Podhaler continued to take dornase alfa, bronchodilators, inhaled corticosteroids, and macrolides. No clinical signs of drug interactions with these medicines were identified.

Concurrent and/or sequential use of TOBI Podhaler with other drugs with neurotoxic, nephrotoxic, or ototoxic potential should be avoided.

Some diuretics can enhance aminoglycoside toxicity by altering antibiotic concentrations in serum and tissue. TOBI Podhaler should not be administered concomitantly with ethacrynic acid, furosemide, urea, or intravenous mannitol. The interaction between inhaled mannitol and TOBI Podhaler has not been evaluated.

8 USE IN SPECIFIC POPULATIONS

8.1 Pregnancy

Risk Summary

Aminoglycosides can cause fetal harm. Published literature reports that use of streptomycin, an aminoglycoside, can cause total, irreversible, bilateral congenital deafness when administered to a pregnant woman [Warnings and Precautions (5.5)]. Although there are no available data on TOBI Podhaler use in pregnant women to inform a drug-associated risk of major birth defects, miscarriage or adverse maternal or fetal outcomes, systemic absorption of tobramycin following inhaled administration is expected to be minimal [see Clinical Pharmacology (12.3)]. There are risks to the mother associated with cystic fibrosis in pregnancy (see Clinical Considerations). In animal reproduction studies with subcutaneous administration of tobramycin in pregnant rats and rabbits during organogenesis there were no adverse developmental outcomes; however, ototoxicity was not evaluated in the offspring from these studies (see Data). Advise pregnant women of the potential risk to a fetus.

The estimated background risk of major birth defects and miscarriage for the indicated populations are unknown. All pregnancies have a background risk of birth defect, loss, or other adverse outcomes. In the U.S. general population, the estimated background risk of major birth defects and miscarriage in clinically recognized pregnancies is 2% to 4% and 15% to 20%, respectively.

Clinical Considerations

Disease-Associated Maternal and/or Embryo/Fetal Risk

Cystic fibrosis may increase the risk for preterm delivery.

Data

Animal Data

No reproduction toxicology studies have been conducted with TOBI Podhaler. However, subcutaneous administration of tobramycin at doses of up to 100 (rat) or 20 (rabbit) mg/kg/day during organogenesis was not associated with adverse developmental outcomes. Doses of tobramycin ≥40 mg/kg/day were severely maternally toxic to rabbits and precluded the evaluation of adverse developmental outcomes. Ototoxicity was not evaluated in offspring during non-clinical reproductive toxicity studies with tobramycin.

8.2 Lactation

Risk Summary

There are no data on the presence of tobramycin following administration of TOBI Podhaler in either human or animal milk, the effects on the breastfed infant, or the effects on milk production. Limited published data on other formulations of tobramycin in lactating women indicate that tobramycin is present in human milk. However, systemic absorption of tobramycin following inhaled administration is expected to be minimal [see Clinical Pharmacology (12.3)]. Tobramycin may cause alteration in the intestinal flora of the breastfeeding infant (see Clinical Considerations). The developmental and health benefits of breastfeeding should be considered along with the mother's clinical need for TOBI Podhaler and any potential adverse effects on the breastfed infant from TOBI Podhaler or from the underlying maternal condition.

Clinical Considerations

Tobramycin may cause intestinal flora alteration. Advise a woman to monitor the breastfed infant for loose or bloody stools and candidiasis (thrush, diaper rash).

8.4 Pediatric Use

Patients 6 years and older were included in the Phase 3 studies with TOBI Podhaler; 206 patients below 20 years of age received TOBI Podhaler. No dosage adjustments are needed based on age. The overall pattern of adverse events in pediatric patients was similar to the adults. Dysgeusia (taste disturbance) was more commonly reported in younger patients six to 19 years of age than in patients 20 years and older, 7.4% versus 2.7%, respectively. Safety and effectiveness in pediatric patients below the age of 6 years have not been established.

8.5 Geriatric Use

Clinical studies of TOBI Podhaler did not include sufficient numbers of subjects aged 65 years and over to determine whether they respond differently from younger subjects. Tobramycin is known to be substantially excreted by the kidney, and the risk of adverse reactions to this drug may be greater in patients with impaired renal function. Because elderly patients are more likely to have decreased renal function, it may be useful to monitor renal function [see Warnings and Precautions (5.2, 5.5)].

8.6 Renal Impairment

Tobramycin is primarily excreted unchanged in the urine and renal function is expected to affect the exposure to tobramycin. The risk of adverse reactions to this drug may be greater in patients with impaired renal function. Patients with serum creatinine ≥2 mg/dL and blood urea nitrogen (BUN) ≥40 mg/dL have not been included in clinical studies and there are no data in this population to support a recommendation regarding dose adjustment with TOBI Podhaler [see Warnings and Precautions (5.2, 5.5)].

8.7 Hepatic Impairment

No studies have been performed in patients with hepatic impairment. As tobramycin is not metabolized, an effect of hepatic impairment on the exposure to tobramycin is not expected.

8.8 Organ Transplantation

Adequate data do not exist for the use of TOBI Podhaler in patients after organ transplantation.

10 OVERDOSAGE

The maximum tolerated daily dose of TOBI Podhaler has not been established.

In the event of accidental oral ingestion of TOBI Podhaler capsules, systemic toxicity is unlikely as tobramycin is poorly absorbed. Tobramycin serum concentrations may be helpful in monitoring overdosage.

Acute toxicity should be treated with immediate withdrawal of TOBI Podhaler, and baseline tests of renal function should be undertaken.

Hemodialysis may be helpful in removing tobramycin from the body.

In all cases of suspected overdosage, physicians should contact the Regional Poison Control Center for information about effective treatment. In the case of any overdosage, the possibility of drug interactions with alterations in drug disposition should be considered.

11 DESCRIPTION

TOBI Podhaler consists of a dry powder formulation of tobramycin for oral inhalation only with the Podhaler device. The inhalation powder is filled into clear, colorless hypromellose capsules.

Each clear, colorless hypromellose capsule contains a spray dried powder of 28 mg of tobramycin active ingredient with 1,2-distearoyl-sn-glycero-3-phosphocholine (DSPC), calcium chloride, and sulfuric acid (for pH adjustment).

The active component of TOBI Podhaler is tobramycin. Tobramycin is an aminoglycoside antibiotic. Its chemical name is O-3-amino-3-deoxy-α-D-glucopyranosyl-(1→4)-O-[2,6-diamino-2,3,6-trideoxy-α-D-ribo-hexopyranosyl-(1→6)]-2-deoxy-L-streptamine; its structural formula is:

Tobramycin has a molecular weight of 467.52, and its empirical formula is C18H37N5O9. Tobramycin is a white to almost white powder; visually free from any foreign contaminants. Tobramycin is freely soluble in water, very slightly soluble in ethanol, and practically insoluble in chloroform and ether.

The Podhaler device is a plastic device used to inhale the dry powder contained in the TOBI Podhaler capsule. Under standardized in vitro testing at a fixed flow rate of 60 L/min and volume of 2 L for 2 seconds, the Podhaler device has a target delivered dose of 102 mg of tobramycin from the mouthpiece (4 capsules per dose). Peak inspiratory flow rate and inhaled volumes were explored in 96 cystic fibrosis patients aged 6 years and older. Older patients with significant disease progression and associated decreases in forced expiratory volume (FEV1) and younger patients with inhaled volumes <1 L were able to generate inspiratory flow rates and volumes required to receive their medication when following the instructions for use. However, no pediatric patients aged 6 to 10 years with FEV1 less than 40% predicted were evaluated.

12 CLINICAL PHARMACOLOGY

12.1 Mechanism of Action

Tobramycin is an aminoglycoside antibacterial [see Clinical Pharmacology (12.4)].

12.3 Pharmacokinetics

Absorption

TOBI Podhaler contains tobramycin, a cationic polar molecule that does not readily cross epithelial membranes. TOBI Podhaler is specifically formulated for administration by oral inhalation. The systemic exposure to tobramycin after inhalation of TOBI Podhaler is expected to result from pulmonary absorption of the dose fraction delivered to the lungs as tobramycin and is not absorbed to any appreciable extent when administered via the oral route.

Serum Concentrations

After inhalation of a 112 mg single dose (4 times 28 mg capsules) of TOBI Podhaler in cystic fibrosis patients, the maximum serum concentration (Cmax) of tobramycin was 1.02 ± 0.53 mcg/mL (mean ± SD) and the median time to reach the peak concentration (Tmax) was 1 hour. In comparison, after inhalation of a single 300 mg dose of TOBI, Cmax was 1.04 ± 0.58 mcg/mL and median Tmax was 1 hour. The extent of systemic exposure (AUC0-12) was also similar: 4.6 ± 2.0 mcg∙h/mL following the 112 mg TOBI Podhaler dose and 4.8 ± 2.5 mcg∙h/mL following the 300 mg TOBI dose. At the end of a 4-week dosing cycle of TOBI Podhaler (112 mg twice-daily), the maximum serum concentration of tobramycin 1 hour after dosing ranged from 1.48 ± 0.69 mcg/mL to 1.99 ± 0.59 mcg/mL (mean ± SD).

Sputum Concentrations

After inhalation of a 112 mg single dose (4 times 28 mg capsules) of TOBI Podhaler in cystic fibrosis patients, sputum Cmax of tobramycin was 1048 ± 1080 mcg/g (mean ± SD). In comparison, after inhalation of a single 300 mg dose of TOBI, sputum Cmax was 737 ± 1028 mcg/g. The variability in pharmacokinetic parameters was higher in sputum as compared to serum.

Distribution

A population pharmacokinetic analysis for TOBI Podhaler in cystic fibrosis patients estimated the apparent volume of distribution of tobramycin in the central compartment to be 85.1 L for a typical cystic fibrosis (CF) patient.

Binding of tobramycin to serum proteins is negligible.

Metabolism

Tobramycin is not metabolized and is primarily excreted unchanged in the urine.

Elimination

Tobramycin is eliminated from the systemic circulation primarily by glomerular filtration of the unchanged compound. Systemically absorbed tobramycin following TOBI Podhaler administration is also expected to be eliminated principally by glomerular filtration.

The apparent terminal half-life of tobramycin in serum after inhalation of a 112 mg single dose of TOBI Podhaler was approximately 3 hours in cystic fibrosis patients and consistent with the half-life of tobramycin after TOBI inhalation.

A population pharmacokinetic analysis for TOBI Podhaler in cystic fibrosis patients aged 6 to 58 years estimated the apparent serum clearance of tobramycin to be 14.5 L/h. No clinically relevant covariates that were predictive of tobramycin clearance were identified from this analysis.

12.4 Microbiology

Mechanism of Action

Tobramycin is an aminoglycoside antibacterial produced by Streptomyces tenebrarius. It acts primarily by disrupting protein synthesis leading to altered cell membrane permeability, progressive disruption of the cell envelope, and eventual cell death.

Tobramycin has in vitro activity against Gram-negative bacteria including P. aeruginosa. It is bactericidal in vitro at peak concentrations equal to or slightly greater than the minimum inhibitory concentration (MIC).

Susceptibility Testing

Interpretive criteria for inhaled antibacterial products are not defined. The in vitro antimicrobial susceptibility test methods used to determine the susceptibility for parenteral tobramycin therapy can be used to monitor the susceptibility of P. aeruginosa isolated from cystic fibrosis patients. (1,2,3) The relationship between in vitro susceptibility test results and clinical outcome with TOBI Podhaler therapy is not clear. A single sputum sample from a cystic fibrosis patient may contain multiple morphotypes of P. aeruginosa and each morphotype may require a different concentration of tobramycin to inhibit its growth in vitro. Patients should be monitored for changes in tobramycin susceptibility.

Development of Resistance

In clinical studies, some increases from baseline to the end of the treatment period were observed in the tobramycin MIC for P. aeruginosa morphotypes. In general, a higher percentage of patients treated with TOBI Podhaler had increases in tobramycin MIC compared with placebo or patients treated with TOBI inhalation solution.

The clinical significance of changes in MICs for P. aeruginosa has not been clearly established in the treatment of cystic fibrosis patients.

Cross-Resistance

Some emerging resistance to aztreonam, ceftazidime, ciprofloxacin, imipenem, or meropenem were observed in the TOBI Podhaler clinical trials. As other anti-pseudomonal antibiotics were concomitantly utilized in many patients in the clinical trials, the association with TOBI Podhaler is not clear.

Other

No trends were observed in the isolation of treatment-emergent bacterial respiratory pathogens (Burkholderia cepacia, Stenotrophomonas maltophilia, Staphylococcus aureus, and Achromobacter xylosoxidans).

13 NONCLINICAL TOXICOLOGY

13.1 Carcinogenesis, Mutagenesis, Impairment of Fertility

Carcinogenicity studies were not conducted with TOBI Podhaler. A 2-year rat inhalation toxicology study to assess carcinogenic potential of TOBI (tobramycin inhalation solution, USP) has been completed. Rats were exposed to TOBI for up to 1.5 hours per day for 95 weeks. Serum levels of tobramycin of up to 35 mcg/mL were measured in rats, in contrast to the maximum 1.99 ± 0.59 mcg/mL level observed in cystic fibrosis patients in TOBI Podhaler clinical trials. There was no drug-related increase in the incidence of any variety of tumor.

Additionally, tobramycin has been evaluated for genotoxicity in a battery of in vitro and in vivo tests. The Ames bacterial reversion test, conducted with 5 tester strains, failed to show a significant increase in revertants with or without metabolic activation in all strains. Tobramycin was negative in the mouse lymphoma forward mutation assay, did not induce chromosomal aberrations in Chinese hamster ovary cells, and was negative in the mouse micronucleus test.

Subcutaneous administration of up to 100 mg/kg of tobramycin did not affect mating behavior or cause impairment of fertility in male or female rats.

14 CLINICAL STUDIES

The Phase 3 clinical development program included two placebo-controlled studies (Studies 2 and 3) and one open-label study (Study 1), which randomized and dosed 157 and 517 patients, respectively, with a clinical diagnosis of cystic fibrosis, confirmed by quantitative pilocarpine iontophoresis sweat chloride test, well-characterized disease causing mutations in each CFTR gene, or abnormal nasal transepithelial potential difference characteristic of cystic fibrosis.

In the placebo-controlled studies, all patients were aged between 6 and 21 years old and had an FEV1 at screening within the range of 25% to 80% (inclusive) of predicted normal values for their age, sex, and height based upon Knudson criteria. In addition, all patients were infected with P. aeruginosa as demonstrated by a positive sputum or throat culture (or bronchoalveolar lavage) within 6 months prior to screening, and also in a sputum culture taken at the screening visit. Among the 76 patients treated with TOBI Podhaler, 37% were males and 63% were females. Thirty-six patients were between 6 and 12 years of age, and 40 patients were between 13 and 21 years of age. Patients had a mean baseline FEV1 of 56% of predicted normal value.

In both studies, >90% of patients received concomitant therapies for cystic fibrosis-related indications. The most frequently used other antibacterial drugs (any route of administration) were azithromycin, ciprofloxacin, and ceftazidime. Consistent with the population of cystic fibrosis patients, the most frequently used concomitant medications included oral pancreatic enzyme preparations, mucolytics (especially dornase alfa), and selective β2-adrenoreceptor agonists.

Study 2

Study 2 was a randomized, 3-cycle, 2-arm trial. Each cycle comprised of 28 days on treatment followed by 28 days off treatment. The first cycle was double-blind, placebo-controlled with eligible patients randomized 1:1 to TOBI Podhaler (4 times 28 mg capsules twice-daily) or placebo. Upon completion of the first cycle, patients who were randomized to the placebo treatment group received TOBI Podhaler for Cycles 2 and 3. The total treatment period was 24 weeks.

A total of 95 patients were randomized into Study 2 and received TOBI Podhaler (n=46) or placebo (n=49) in Cycle 1. All patients were less than 22 years of age (mean age 13.3 years) and had not received inhaled antipseudomonal antibiotics within four months prior to screening; 56% were female and 84% were Caucasian. This study was stopped early for demonstrated benefit and the primary analysis used the set of patients included in the interim analysis (n=79); 16 patients did not have data on the primary endpoint at that time. Of the 79 patients included in the interim analysis, 18 patients were excluded due to a failure to meet spirometry quality review criteria as determined by an external review panel. This resulted in a total of 61 patients, 29 in the TOBI Podhaler arm and 32 in the placebo arm, who were included in the primary analysis.

In the primary analysis, TOBI Podhaler significantly improved lung function compared with placebo as measured by the relative change in FEV1 % predicted from baseline to the end of Cycle 1 dosing. This analysis adjusted for the covariates of baseline FEV1 % predicted, age, and region, and imputed for missing data. Treatment with TOBI Podhaler and placebo resulted in relative increases in FEV1 % predicted of 12.54% and 0.09%, respectively (LS mean difference = 12.44%; 95% CI: 4.89, 20.00; p=0.002). Analysis of absolute changes in FEV1 % predicted showed LS means of 6.38% for TOBI Podhaler and -0.52% for placebo with a difference of 6.90% (95% CI: 2.40, 11.40). Improvements in lung function were achieved during the subsequent cycles of treatment with TOBI Podhaler, although the magnitude was reduced (Figure 1).

The percentage of patients using new antipseudomonal antibiotics in Cycle 1 was greater in the placebo treatment group (18.4%) compared with the TOBI Podhaler treatment group (13.1%). During the first cycle, 8.7% of TOBI Podhaler patients and 10.2% of placebo patients were treated with parenteral antipseudomonal antibiotics. In Cycle 1, two patients (4.4%) in the TOBI Podhaler treatment group required respiratory-related hospitalizations, compared with six patients (12.2%) in the placebo treatment group.

Figure 1 – Study 2: Mean Relative Change in FEV1 % Predicted from Baseline in Cycles 1 to 3 by Treatment Group

Study 3

Study 3 was a randomized, double-blind, placebo-controlled trial, similar in design to Study 2. Eligible patients were randomized 1:1 to receive TOBI Podhaler (4 times 28 mg capsules twice-daily) or placebo for one cycle (28 days on-treatment and 28 days off-treatment).

A total of 62 patients were randomized into Study 3 and allocated to TOBI Podhaler (n=32) or placebo (n=30). All patients were less than 22 years of age (mean age 12.9 years) and had not received inhaled antipseudomonal antibiotics within 4 months prior to screening; 64.5% were female and 98.4% were Caucasian.

In this study, the results were not statistically significant for the primary lung function endpoint when adjusting for the covariates of age (<13 years, ≥13 years) and FEV1 % predicted at screening (<50%, ≥50%) and imputing for missing data. Improvement in lung function for TOBI Podhaler compared with placebo was evaluated using the relative change in FEV1 % predicted from baseline to the end of Cycle 1 dosing. Treatment with TOBI Podhaler (8.19%) compared to placebo (2.27%) failed to achieve statistical significance in relative change in FEV1 % predicted (LS mean difference = 5.91%; 95% CI: -2.54, 14.37; p=0.167). Analyses of absolute changes in FEV1 % predicted showed LS means of 4.86% for TOBI Podhaler and 0.48% for placebo with a difference of 4.38% (95% CI:-0.17, 8.94).

Study 1

Study 1 was a randomized, open-label, active-controlled parallel arm trial. Eligible patients were randomized 3:2 to TOBI Podhaler (4 times 28 mg capsules twice-daily) or TOBI (300 mg/5 mL twice-daily). Treatment was administered for 28 days, followed by 28 days off therapy (one cycle) for three cycles. The total treatment period was 24 weeks. The time to administer a dose of TOBI Podhaler (10th to 90th percentiles) ranged from 2 to 7 minutes at the end of the dosing period for Cycle 1, and 2 to 6 minutes at the end of the dosing period for Cycle 3.

A total of 517 patients were randomized in Study 1 and received TOBI Podhaler (n=308) or TOBI (n=209). Patients were predominantly 20 years of age or older (mean age 25.6 years) with no inhaled antipseudomonal antibiotic use within 28 days prior to study drug administration; 45% were female and 91% were Caucasian.

The primary purpose of Study 1 was to evaluate safety. Interpretation of efficacy results in Study 1 is limited by several factors including open-label design, testing of multiple secondary endpoints, and missing values for the outcome of FEV1 % predicted. The number (%) of patients with missing values for FEV1 % predicted at Weeks 5 and 25 in the TOBI Podhaler treated group were 40 (13.0%) and 86 (27.9%) compared to 15 (7.2%) and 40 (19.1%) in the TOBI treated group. Using imputation of the missing data, the mean differences (TOBI Podhaler minus TOBI) in the percent relative change from baseline in FEV1 % predicted at Weeks 5 and 25 were -0.87 (95% CI: -3.80, 2.07) and 1.62 (95% CI: -0.90, 4.14), respectively.

15 REFERENCES

1. Clinical and Laboratory Standards Institute (CLSI). Methods for Dilution Antimicrobial Susceptibility Tests for Bacteria that Grow Aerobically – Ninth Edition; Approved Standard. CLSI Document M7-A9. CLSI, 950 West Valley Rd., Suite 2500, Wayne, PA 19087, 2012.
2. CLSI. Performance Standards for Antimicrobial Disk Susceptibility Tests; Approved Standard – 11th ed. CLSI document M02-A11. CLSI, 2012.
3. CLSI. Performance Standards for Antimicrobial Susceptibility Testing; 22nd Informational Supplement. CLSI document M100-S22. CLSI, 2012

16 HOW SUPPLIED/STORAGE AND HANDLING

16.1 How Supplied

TOBI Podhaler contains aluminum blister-packaged 28 mg TOBI Podhaler (tobramycin inhalation powder) clear, colorless hypromellose capsules with “MYL TPH” in blue radial imprint on one part of the capsule and the Mylan logo in blue radial imprint on the other part of the capsule, and Podhaler devices.

Each Podhaler device consists of the inhaler body, mouthpiece, capsule chamber and blue push button. The Podhaler device is provided in a case that protects the device during shipment, storage and its one week in-use period.

Unit dose (blister pack), Box of 224 capsules contains: NDC 49502-401-24

4 weekly packs, each containing:
  56 capsules (7 blister cards of 8 capsules)
  1 Podhaler device
1 reserve Podhaler device

Unit dose (blister pack), Box of 56 capsules (7-day pack) contains: NDC 49502-401-56

56 capsules (7 blister cards of 8 capsules)

1 Podhaler device

16.2 Storage and Handling

Store at 25°C (77°F); excursions permitted to 15°C to 30°C (59°F to 86°F)

Protect TOBI Podhaler from moisture.

- TOBI Podhaler capsules should be used with the Podhaler device only. The Podhaler device should not be used with any other capsules.
- Capsules should always be stored in the blister and each capsule should only be removed immediately before use.
- Always use the new Podhaler device provided with each weekly pack.

Keep this and all drugs out of the reach of children.

17 PATIENT COUNSELING INFORMATION

Advise the patient to read the FDA-approved patient labeling (Patient Information and Instructions for Use).

Important Administration Information

Information on the long-term efficacy and safety of TOBI Podhaler is limited. There is no information in patients with limited pulmonary reserve (FEV1 <25% predicted). Decreased susceptibility of Pseudomonas aeruginosa to tobramycin has been seen with use of TOBI Podhaler. The relationship between in vitro susceptibility test results and clinical outcome with TOBI Podhaler therapy is not clear. Occurrence of decreased susceptibility on treatment should be monitored, and treatment with an alternative therapy should be considered if clinical worsening is observed.

TOBI Podhaler may not be tolerated by all patients. Patients should be instructed to consider alternative therapy if they are unable to tolerate TOBI Podhaler. Patients should be advised to complete a full 28-day course of TOBI Podhaler, even if they are feeling better. After 28 days of therapy, patients should stop TOBI Podhaler therapy for the next 28 days, and then resume therapy for the next 28-day on and 28-day off cycle.

Patients should be advised that if they have been prescribed a 7-day pack of TOBI Podhaler either immediately before or during a 28-day treatment with TOBI Podhaler, then they must count each day of use toward the 28 day on-treatment part of their cycle. Patients should only take a total of 28 consecutive days of treatment during a cycle.

Similarly, patients should be advised that if they have been prescribed a 1-day pack of TOBI Podhaler either immediately before or during a 28-day treatment with TOBI Podhaler, then they must count each day of use toward the 28 day on-treatment part of their cycle. Patients should only take a total of 28 consecutive days of treatment during a cycle.

It is important for patients to understand how to correctly administer TOBI Podhaler capsules using the Podhaler device. It is recommended that caregivers and patients be adequately trained in the proper use of the TOBI Podhaler prior to use. [See Instructions for Use at the end of the Patient Information leaflet.] Caregivers should provide assistance to children using TOBI Podhaler (including preparing the dose for inhalation) particularly for those aged 10 years or younger, and should continue to supervise them until they are able to use the Podhaler device properly without help.

For patients taking several different inhaled medications and/or performing chest physiotherapy, advise the patient regarding the order in which they should take the therapies. It is recommended that TOBI Podhaler be taken last.

Difficulty Breathing:

Advise patients to inform their physicians if they experience shortness of breath or wheezing after administration of Tobi Podhaler. Tobi Podhaler can cause a narrowing of the airway [see Warnings and Precautions (5.1)].

Hearing Loss:

Advise patients to inform their physician if they experience ringing in the ears, dizziness, or any changes in hearing because Tobi Podhaler has been associated with hearing loss [see Warnings and Precautions (5.2)].

Kidney Damage:

Advise patients to inform their physician if they have any history of kidney problems because Tobi Podhaler is in a class of drugs that have caused kidney damage [see Warnings and Precautions (5.3)].

Embryo-Fetal Toxicity:

Advise pregnant women that aminoglycosides can cause irreversible congenital deafness when administered to a pregnant woman [see Warnings and Precautions (5.5) and Use in Specific Populations (8.1)].

Lactation:

Advise a woman to monitor their breastfed infants for diarrhea and/or bloody stools [see Use in Specific Populations (8.2)].

Cough:

Inform patients that cough was reported with the use of TOBI Podhaler in clinical trials. If coughing that may be experienced with TOBI Podhaler becomes bothersome or cannot be tolerated, advise patients that tobramycin inhalation solution or alternative therapeutic options may be considered.

Patient Information

TOBI (TOH-bee) Podhaler (POD-hay-ler)

(tobramycin inhalation powder)

for oral inhalation use

Important information: Do not swallow TOBI Podhaler capsules. TOBI Podhaler capsules are used only with the Podhaler device and inhaled through your mouth (oral inhalation). Never place a capsule in the mouthpiece of the Podhaler device.

Read this Patient Information leaflet before you start using TOBI Podhaler and each time you get a refill. There may be new information. This information does not take the place of talking to your healthcare provider about your medical condition or treatment.

What is TOBI Podhaler?

TOBI Podhaler is a prescription medicine used to treat people with cystic fibrosis who have a bacterial infection called Pseudomonas aeruginosa. TOBI Podhaler contains an antibacterial medicine called tobramycin (an aminoglycoside).

It is not known if TOBI Podhaler is safe and effective:

- in children under 6 years of age
- in people who have an FEV1 less than 25% or greater than 80% predicted
- in people who are colonized with a bacterium called Burkholderia cepacia

Who should not use TOBI Podhaler?

Do not use TOBI Podhaler if you are allergic to tobramycin, any of the ingredients in TOBI Podhaler, or to any other aminoglycoside antibacterial medicines.

What should I tell my healthcare provider before using TOBI Podhaler?

Before using TOBI Podhaler, tell your healthcare provider about all of your medical conditions, including if you:

- have or have had hearing problems (including noises in your ears such as ringing or hissing), hearing loss, or your mother has had hearing problems after taking an aminoglycoside.
- have been told you have certain gene variants (a change in the gene) related to hearing abnormalities inherited from your mother.
- have dizziness.
- have or have had kidney problems.
- have or have had problems with muscle weakness such as myasthenia gravis or Parkinson’s disease.
- have or have had breathing problems such as wheezing, coughing, or chest tightness.
- have had an organ transplant.
- are pregnant or plan to become pregnant. TOBI Podhaler contains a medicine that can harm your unborn baby. See “What are the possible side effects of TOBI Podhaler?” for more information.
- are breastfeeding or plan to breastfeed. It is not known if the medicine in TOBI Podhaler (tobramycin inhalation powder) passes into your breast milk.

Tell your healthcare provider about all the medicines you take, including prescription and over-the-counter medicines, vitamins, and herbal supplements.

Using TOBI Podhaler with certain other medicines can cause serious side effects. Ask your healthcare provider or pharmacist for a list of these medicines, if you are not sure. Know the medicines you take. Keep a list of them and show it to your healthcare provider and pharmacist when you get a new medicine.

If you are using TOBI Podhaler, you should discuss with your healthcare provider if you should take:

- other medicines that may harm your nervous system, kidneys, or hearing
- “water pills” (diuretics) such as Edecrin (ethacrynic acid), Lasix (furosemide), or intravenous mannitol
- urea

How should I use TOBI Podhaler?

- See the step-by-step Instructions for Use at the end of this Patient Information leaflet about the right way to use TOBI Podhaler. Do not use TOBI Podhaler unless your healthcare provider has taught you how to use it the right way.
- Use TOBI Podhaler exactly as your healthcare provider tells you to use it. Ask your healthcare provider or pharmacist if you are not sure.
- The usual dose for adults and children over 6 years of age is:
  - The contents of 4 TOBI Podhaler capsules inhaled by mouth in the morning using your Podhaler device and the contents of 4 TOBI Podhaler capsules inhaled by mouth in the evening using your Podhaler device.
  - Check to see that each capsule is empty after inhaling. If powder remains in the capsule, repeat inhalation until the capsule is empty.
- Each dose of 4 TOBI Podhaler capsules should be taken as close to 12 hours apart as possible.
- You should not take your dose of 4 TOBI Podhaler capsules less than 6 hours apart.
- After using TOBI Podhaler for 28 days, you should stop using it and wait 28 days. After you have stopped using TOBI Podhaler for 28 days, you should start using TOBI Podhaler again for 28 days. Complete the full 28-day course even if you are feeling better. It is important that you keep to the 28-day on, 28-day off cycle (See Figure A).

(Figure A)

- If you have been prescribed a 7-day pack of TOBI Podhaler either immediately before or during a 28-day treatment with TOBI Podhaler, then you must count each day of use toward the 28-day on-treatment part of the cycle. You should only take a total of 28 consecutive days of treatment during a cycle.
- If you have been prescribed a 1-day pack of TOBI Podhaler either immediately before or during a 28-day treatment with TOBI Podhaler, then you must count each day of use toward the 28-day on-treatment part of the cycle. You should only take a total of 28 consecutive days of treatment during a cycle.
- If you are taking other medicines inhaled through your mouth, your healthcare provider will tell you how to take your medicines the right way.
- If you are doing therapies for cystic fibrosis (chest physiotherapy), you should use TOBI Podhaler after your other therapies are done.
- If you inhale too much TOBI Podhaler, tell your healthcare provider right away.
- If you accidentally swallow TOBI Podhaler capsules, tell your healthcare provider right away.
- Use a new TOBI Podhaler device every 7 days.
- Caregivers should help children who are 10 years of age and younger use TOBI Podhaler, and keep watching them use their TOBI Podhaler until they are able to use it the right way without help.
- Tell your doctor if your symptoms worsen while using your TOBI Podhaler.

What are the possible side effects of TOBI Podhaler?

TOBI Podhaler can cause serious side effects, including:

- severe breathing problems (bronchospasm). Tell your healthcare provider right away if you get any of these symptoms of bronchospasm while using TOBI Podhaler:
  - shortness of breath with wheezing
  - coughing and chest tightness
- hearing loss or ringing in the ears (ototoxicity). Tell your healthcare provider right away if you have hearing loss or hear noises in your ears such as ringing or hissing, or if you develop vertigo, difficulty with balance or dizziness.
- worsening kidney problems (nephrotoxicity). TOBI Podhaler is in a class of medicines which may cause worsening kidney problems, especially in people with known or suspected kidney problems. Your healthcare provider may do a blood test to check how your kidneys are working while you are using TOBI Podhaler.
- worsening muscle weakness. TOBI Podhaler is in a class of medicines which can cause muscle weakness to get worse in people who already have problems with muscle weakness (myasthenia gravis or Parkinson’s disease).
- The medicine in TOBI Podhaler is in a class of medicines which may cause harm to an unborn baby.

The most common side effects of TOBI Podhaler include:

- cough
- worsening of lung problems or cystic fibrosis
- productive cough

- shortness of breath
- fever
- sore throat
- changes in your voice (hoarseness)

- coughing up blood
- headache

Let your healthcare provider know if your symptoms get worse. Some patients may not be able to continue using TOBI Podhaler and need to consider other treatments. Tell your healthcare provider about any side effect that bothers you enough to stop treatment or that does not go away.

These are not all of the possible side effects of TOBI Podhaler. Call your doctor for medical advice about side effects. You may report side effects to FDA at 1-800-FDA-1088.

General information about the safe and effective use of TOBI Podhaler.

Medicines are sometimes prescribed for purposes other than those listed in a Patient Information leaflet. Do not use TOBI Podhaler for a condition for which it was not prescribed. Do not give TOBI Podhaler to other people, even if they have the same problem you have. It may harm them.

You can ask your healthcare provider or pharmacist for information about TOBI Podhaler that was written for healthcare professionals.

For more information, go to www.TOBIPodhaler.com or call 1-877-999-TOBI (8624).

What are the ingredients in TOBI Podhaler?

Active ingredient: tobramycin

Inactive ingredients: 1,2-distearoyl-sn-glycero-3-phosphocholine (DSPC), calcium chloride, and sulfuric acid (for pH adjustment)

INSTRUCTIONS FOR USE

TOBI (TOH-bee) Podhaler (POD-hay-ler)

(tobramycin inhalation powder)

Important Information:

- Your healthcare provider should show you or a caregiver how to use TOBI Podhaler the right way before you use it for the first time. Ask your healthcare provider if you have any questions about how to use TOBI Podhaler the right way.
- The recommended dose of TOBI Podhaler is the contents of 4 capsules inhaled by mouth 2 times each day.
- TOBI Podhaler comes in a blister card. Each blister card has 8 TOBI Podhaler capsules: 4 capsules for inhalation in the morning and 4 capsules for inhalation in the evening.
- You must inhale all of the powdered medicine from all 4 TOBI Podhaler capsules to get the full dose. If all of the powdered TOBI Podhaler medicine is not inhaled, you will not get the full dose.
  - After you have inhaled 2 times from a capsule, remove the capsule from the capsule chamber and hold the used capsule up to the light and look through it. It should be empty with only a fine coating of powder left on the inside surface of the capsule (See Figure S).
    - If the capsule is empty, throw it away and continue following the Instructions for Use.
    - If the capsule is not empty, see the section “What to do with a capsule that has not been emptied” below for instructions.
- You or a caregiver should tell your healthcare provider as soon as possible if you think you or your child has not received the full TOBI Podhaler dose. Your healthcare provider should show you how to use TOBI Podhaler the right way.
  Follow the instructions below for using your TOBI Podhaler. You will breathe in (inhale) the medicine in the TOBI Podhaler capsules using the Podhaler device. If you have any questions, ask your healthcare provider or pharmacist.
  TOBI Podhaler is available as a 28-day, 7-day, and 1-day supply package.
  Each TOBI Podhaler package contains (See Figure A):
  - 4 weekly packs (28-day supply), each containing:
    - 56 capsules (7 blister cards of 8 capsules). Each blister card contains 8 TOBI Podhaler capsules (4 capsules for inhalation in the morning and 4 capsules for inhalation in the evening).
    - 1 Podhaler device and its storage case.
      and
    - 1 extra (reserve) Podhaler device (to be used if needed) and its storage case.
Or:
  1. 7-day pack (7-day supply) containing:
    - 56 capsules (7 blister cards of 8 capsules). Each blister card contains 8 TOBI Podhaler capsules (4 capsules for inhalation in the morning and 4 capsules for inhalation in the evening).
    - 1 Podhaler device and its storage case.
Or:
  1. 1-day pack (1-day supply) containing:
    - 8 capsules (1 blister card of 8 capsules). Each blister card contains 8 TOBI Podhaler capsules (4 capsules for inhalation in the morning and 4 capsules for inhalation in the evening).
    - 1 Podhaler device and its storage case.

Note:

- Do not swallow TOBI Podhaler capsules. The powder in the capsule is for you to inhale using the Podhaler device.
- Only use the Podhaler device that comes in the pack. Do not use TOBI Podhaler capsules with any other device, and do not use the Podhaler device to take any other medicine.
- When you start a new weekly (7-day) pack of capsules, use the new Podhaler device that is supplied in the pack and throw away (discard) the used device and its storage case. Each Podhaler device is only used for 1 week (7 days).
- Always keep the TOBI Podhaler capsules in the blister card. Only remove 1 capsule at a time just before you are going to use it.
- Doses should be inhaled as close to 12 hours apart as possible and not less than 6 hours apart.
- Small pieces of the capsules can get into your mouth and you may be able to feel these pieces on your tongue. These small pieces will not hurt you if you swallow or inhale them.
- The extra (reserve) Podhaler device provided in the 28-day supply package may be used if the Podhaler device:
  - is wet, dirty, or broken
  - has been dropped
  - does not seem to be piercing the capsule properly (see Step 17)

Getting ready:

- Wash and dry your hands (See Figure B).

Preparing your TOBI Podhaler dose

Your Podhaler device comes in a storage case with a lid. The device has a removable mouthpiece, capsule chamber and a button at its base (See Figure C).

Step 1: Just before use, hold the base of the storage case and unscrew the lid by turning it to the left (counter-clockwise) (See Figure D). Set the lid aside.

Step 2: Leave the Podhaler device in the base of the storage case while you prepare your dose (See Figure E).

Step 3: Hold the body of the Podhaler device and unscrew the mouthpiece by turning it to the left (counter-clockwise direction) (See Figure F). Set the mouthpiece aside on a clean, dry surface.

Note: Each blister card contains 8 TOBI Podhaler capsules: 4 capsules for inhalation in the morning and 4 capsules for inhalation in the evening.

Step 4: Take 1 blister card and tear the pre-cut lines along the length (See Figure G) then tear at the pre-cut lines along the width (See Figure H).

Step 5: Peel (by rolling back) the foil that covers 1 TOBI Podhaler capsule on the blister card (See Figure I). Always hold the foil close to where you are peeling.

Step 6: Take out 1 TOBI Podhaler capsule from the blister card (See Figure J). Note: Only peel back the foil from 1 capsule at a time and remove the capsule just before you are going to use it in the device because the blister protects the capsule from moisture.

Step 7: Place the TOBI Podhaler capsule in the capsule chamber at the top of the Podhaler device right away (See Figure K). Do not put the capsule directly into the top of the mouthpiece.

Step 8: Put the mouthpiece back on your Podhaler device and screw the mouthpiece on by turning it to the right (clockwise) until it is tight (See Figure L). Do not overtighten.

Step 9: Remove the Podhaler device from the base of the case. Hold the Podhaler device with the mouthpiece pointing down. Put your thumb on the blue button and press the blue button all the way down (See Figure M). Let go of the blue button. Do not press the blue button more than 1 time. The chances of the capsule breaking into pieces will be increased if the capsule is accidentally pierced (a hole put in it) more than 1 time.

Taking your TOBI Podhaler dose

Note: You will need to repeat Step 10 to Step 14 for each capsule so you inhale each capsule 2 times to empty the capsule.

Step 10: Breathe out (exhale) all the way (See Figure N). Do not blow or exhale into the mouthpiece.

Step 11: Place your mouth over the mouthpiece and close your lips tightly around it (See Figure O).

Step 12: Inhale deeply with a single breath (See Figure P).

Step 13: Remove the Podhaler device from your mouth and hold your breath for about 5 seconds.

Step 14: Exhale and take a few normal breaths away from the Podhaler device. Do not blow or exhale into the mouthpiece.

Step 15: Repeat Step 10 through Step 14 using the same capsule.

- You must inhale 2 times from each capsule to empty it.

Step 16: Unscrew the mouthpiece by turning it to the left (counterclockwise) and remove the TOBI Podhaler capsule from the capsule chamber (See Figure Q and Figure R below).

Step 17: Hold the used capsule up to the light and look through it. It should be empty with only a fine coating of powder remaining on the inside surface of the capsule (See Figure S). If the capsule is empty, throw it away and go to Step 18.

If the capsule is not empty, see “What to do with a capsule that has not been emptied” below for instructions.

What to do with a capsule that has not been emptied:

- If the capsule is pierced but still contains more than just a fine coating of powder (See Figure T) you must inhale from it again 2 times:
  - Put the capsule back into the Podhaler device capsule chamber with the pierced side of the capsule pointing down.
  - Screw the mouthpiece back on the Podhaler device by turning it to the right (clockwise) until it is tight.
  - Repeat Step 10 to Step 17.

- If the capsule is not pierced (See Figure U) you must pierce it again and inhale from it 2 times:
  - Put the capsule back into the Podhaler device capsule chamber.
  - Screw the mouthpiece back on the Podhaler device by turning it to the right (clockwise) until it is tight.
  - Repeat Step 9 to Step 17 making sure to press the blue button all the way down.

Note: If you have tried to pierce the capsule 2 times and it is still not pierced, use the extra (reserve) Podhaler device provided in the TOBI Podhaler package instead (only available in the 28-day supply package). If you need a new device, ask your healthcare provider.

  - Prepare the extra (reserve) Podhaler device by following Step 1 to Step 3.
  - Then using the same capsule, repeat Step 7 to Step 17.

Step 18: Repeat Step 5 to Step 17 for 3 more times until your full dose (4 capsules) has been taken (See Figure V).

After your TOBI Podhaler dose:

Step 19: Do not store the TOBI Podhaler capsules in the Podhaler device.

Step 20: Put the mouthpiece back on to your Podhaler device and screw the mouthpiece on by turning it to the right (clockwise) until it is tight (See Figure L). Do not overtighten.

Step 21: Wipe the mouthpiece with a clean, dry cloth (See Figure W).

- Do not wash the Podhaler device with water. Your Podhaler device needs to stay dry at all times to work the right way.

Step 22: Place your Podhaler device back in the storage case base.

Step 23: Place the lid back on the storage case base and screw the cover on by turning it to the right (clockwise) until it is tight (See Figure X).

How should I store TOBI Podhaler?

- Store your Podhaler device and blister-packaged capsules at room temperature between 68°F to 77°F (20°C to 25°C).
- Keep the TOBI Podhaler capsules and Podhaler device in a dry place.
- Store the Podhaler device tightly closed in its storage case when you are not using it.
- Keep TOBI Podhaler capsules, Podhaler device, and all medicines out of the reach of children.

This Patient Information and Instructions for Use have been approved by the U.S. Food and Drug Administration.

© 2020 Mylan Inc.

Tobi® and Podhaler® are registered trademarks of BGP Products Operations GmbH, a Mylan company.

Manufactured for:
Mylan Specialty L.P.
Morgantown, WV 26505 U.S.A.

Manufactured by:
Mylan Pharmaceuticals Inc.
150 Industrial Road
San Carlos, CA 94070 U.S.A.

Revised: 2/2023
N:TOBRIP:R4/PI:TOBRIP:R4/IFU:TOBRIP:R2

PRINCIPAL DISPLAY PANEL – 28 mg

NDC 49502-401-24 Rx only

TOBI® Podhaler®
(tobramycin inhalation powder)

28 mg per capsule

For Oral Inhalation Only

Do not swallow TOBI® Podhaler® capsules

TOBI® Podhaler® capsules are for use with the Podhaler® device only

This package contains a 4-week supply of capsules:
4 weekly packs x 56 capsules per pack

Each capsule contains 28 mg tobramycin with 1,2-distearoyl-sn-glycero-3-phosphocholine (DSPC), calcium chloride, and sulfuric acid (for pH adjustment)

Dosage: See prescribing information.
Store at 25°C (77°F); excursions permitted to 15-30°C (59-86°F); protect from moisture.

Capsules Should Always Be Stored in the Blister and Only Removed Immediately Before Use.

Always store the Podhaler® device in its case.

Keep this and all drugs out of the reach of children.

Contents:
4 weekly packs, each containing:
56 capsules (7 blister cards of 8 capsules)
1 Podhaler® device
Patient information leaflet
1 Reserve Podhaler® device
Prescribing Information

Product of Hungary

Manufactured for:
Mylan Specialty L.P.
Morgantown, WV 26505 U.S.A.

Manufactured by:
Mylan Pharmaceuticals Inc.
San Carlos, CA 94070 U.S.A.

© 2020 Mylan Inc.

GTIN: 00349502401244
EXP/LOT